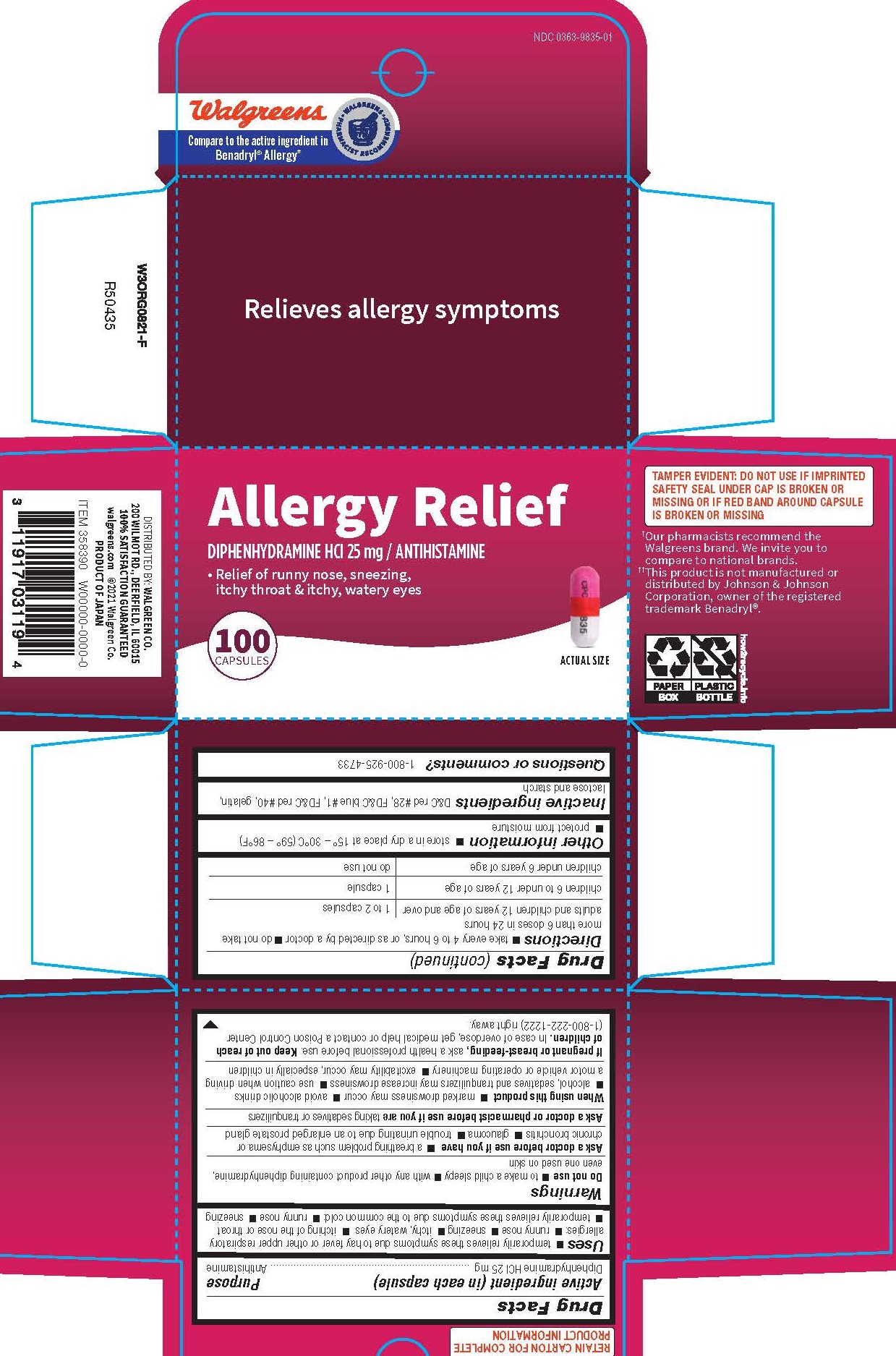 DRUG LABEL: Diphenhydramine Hydrochloride
NDC: 0363-9835 | Form: CAPSULE
Manufacturer: Walgreen Company
Category: otc | Type: HUMAN OTC DRUG LABEL
Date: 20241206

ACTIVE INGREDIENTS: DIPHENHYDRAMINE HYDROCHLORIDE 25 mg/1 1
INACTIVE INGREDIENTS: GELATIN; FD&C RED NO. 40; D&C RED NO. 28; FD&C BLUE NO. 1; LACTOSE MONOHYDRATE; STARCH, CORN

0835 - Walgreen

Drug Facts

Active ingredient (in each capsule)

Diphenhydramine HCI 25 mg

Purpose

Antihistamine

Uses

 temporarily relieves these symptoms due to hay fever or other upper respiratory allergies:  runny nose  sneezing  itchy, watery eyes  itching of the nose or throat
 temporarily relieves these symptoms due to the common cold:  runny nose  sneezing

WARNINGS

Do not use

 to make a child sleepy

 with any other product containing diphenhydramine, even one used on skin

Ask a doctor before use if you have

 a breathing problem such as emphysema or chronic bronchitis

 glaucoma

 trouble urinating due to an enlarged prostate gland

Ask a doctor or pharmacist before use ifyou are taking sedatives or tranquilizers

When using this product

 marked drowsiness may occur

 avoid alcoholic drinks
 alcohol, sedatives and tranquilizers may increase drowsiness

 use caution when driving a motor vehicle or operating machinery

 excitability may occur, especially in children

PREGNANCY OR BREAST FEEDING

If pregnant or breast-feeding, ask a health professional before use.

Keep out of reach of children.

OVERDOSAGE

In case of overdose, get medical help or contact a Poison Control Center (1-800-222-1222) right away.

Directions

 take every 4 to 6 hours, or as directed by a doctor

 do not take more than 6 doses in 24 hours

adults and children 12 years of age and over | 1 to 2 capsules
children 6 to under 12 years of age | 1 capsule
children under 6 years of age | do not use

Other information

 store in a dry place at 15° – 30°C (59° – 86°F)
 protect from moisture

INACTIVE INGREDIENT

D&C red #28, FD&C blue #1, FD&C red #40, gelatin, lactose and starch

Questions or comments?

1-800-925-4733

DISTRIBUTED BY: WALGREEN CO.
200 WILMOT RD., DEERFIELD, IL 60015
100% SATISFACTION GUARANTEED
walgreens.com ©2021 Walgreen Co.
PRODUCT OF JAPAN

TAMPER EVIDENT: DO NOT USE IF IMPRINTED SAFETY SEAL UNDER CAP IS BROKEN OR MISSING OR IF RED BAND AROUND CAPSULE IS BROKEN OR MISSING

†Our pharmacists recommend the Walgreens brand. We invite you to compare to national brands

††This product is not manufactured or distributed by Johnson & Johnson Corporation, owner of the registered trademark Benadryl®

PACKAGE LABEL

Walgreens

Compare to the active ingredient in Benadryl® Allergy††

NDC 0363-9835-01

Relieves allergy symptoms

Allergy Relief

Diphenhysramine HCl 25 mg / Antihistamine

Relief of runny nose, sneezing, itchy throat & itchy, watery eyes

100 Capsules